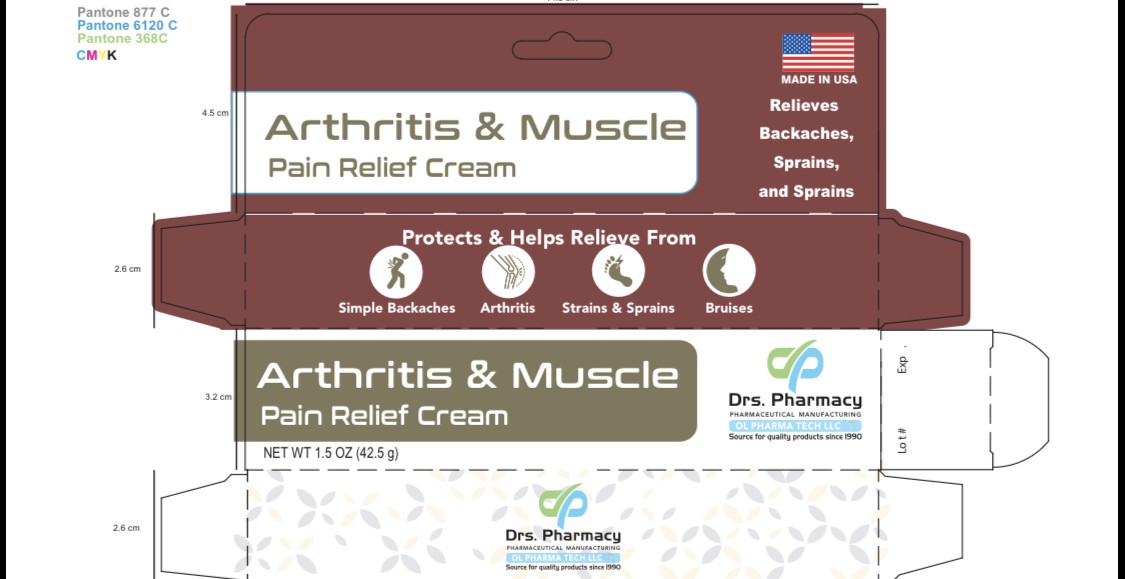 DRUG LABEL: Drs Pharmacy PAIN RELIEF  MUSCLE  ARITHRITIS
NDC: 80489-099 | Form: CREAM
Manufacturer: OL PHARMA TECH,LLC
Category: otc | Type: HUMAN OTC DRUG LABEL
Date: 20260130

ACTIVE INGREDIENTS: CAPSAICIN 0.025 g/100 g
INACTIVE INGREDIENTS: CETEARETH-12; PROPYLENE GLYCOL; METHYLPARABEN; EDETATE DISODIUM; TROLAMINE; SODIUM CETOSTEARYL SULFATE; PROPYLPARABEN; WATER; CETOSTEARYL ALCOHOL; MINERAL OIL; .ALPHA.-TOCOPHEROL; STEARIC ACID

ACTIVE INGREDIENT

capsaicin 0.025%

PURPOSE

PAIN RELIEF

USES

for the temporary relief of minor aches and pains of muscles and joints associated with :

- simple back aches
- arithriris
- strains
- sprains

WARNINGS

For external use only

- do not apply to wounds or damaged skin
- do not bandage tightly
- do not use with heating pads/pack/wrap/hot water bottle or any heating elements

DO NOT USE

for external feminine itching if you have a vaginal discharge. Consult a doctor.
for the treatment of diaper rash. Consult a doctor.

WHEN USING THIS PRODUCT

•avoid contact with the eyes

- avoid contact with other mucos membranes

STOP USE AND ASK YOUR DOCTOR IF

•the condition gets worse

• symptoms persist more than 7 days or clear up and occur again within a few days.

Keep out of reach of children. If swallowed, get medical help or contact a Poison Control Center right away.

if pregnent or nursing see the advice of health care proffessional before using.

DIRECTIONS

Children under 12 years of age consult a physician
Apply a thin layer to affected area not more than 3 to 4 times daily
Gently massage into the skin until fully absorbed
Wash hands with soap and water after each application to avoid spreading to the eyes or other sensitive mucous membranes
A burning sensation may occur upon initial application but generally disappears with continued use
For a severe burning discomfort, remove excess product wiht a soft cloth and mineral oil

OTHER INFORMATION

- Store at room temperature 59°-86°F (15°-30°C).
- Protect from freezing.
- Before using any medication, read all label directions. Keep carton, it contains important information.

INACTIVE INGREDIENTS

cetostearyl alcohol, sodium cetostearyl sulfate, stearic acid, trolamine, mineral oil , propylene glycol, water, methyl paraben, propyl paraben, EDTA, vitamin E

QUESTIONS

CALL : 248-325-4231